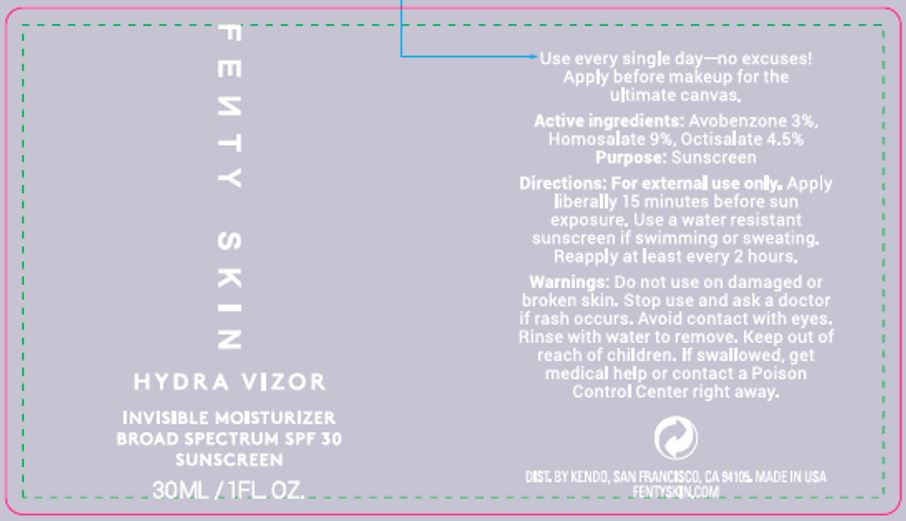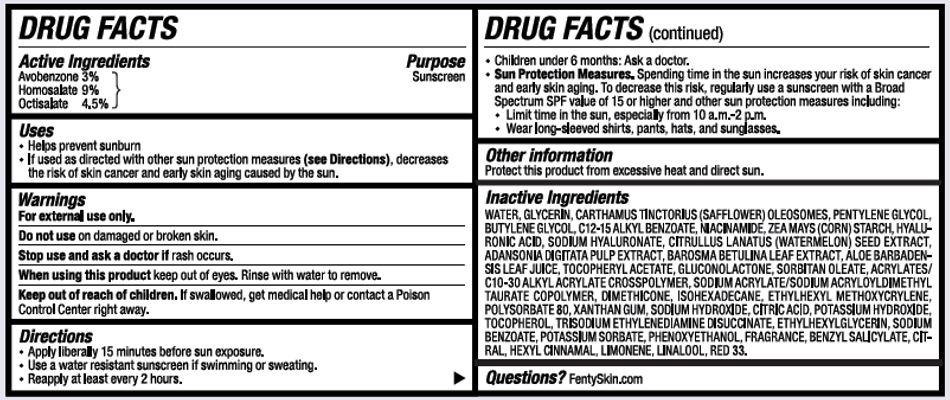 DRUG LABEL: FENTY SKIN HYDRA VIZOR
NDC: 71499-220 | Form: LOTION
Manufacturer: KENDO HOLDINGS INC
Category: otc | Type: HUMAN OTC DRUG LABEL
Date: 20250930

ACTIVE INGREDIENTS: AVOBENZONE 3 g/100 mL; HOMOSALATE 9 g/100 mL; OCTISALATE 4.5 g/100 mL
INACTIVE INGREDIENTS: ADANSONIA DIGITATA FRUIT PULP; HYALURONIC ACID; HYALURONATE SODIUM; D&C RED NO. 33; POTASSIUM SORBATE; TOCOPHEROL; BENZYL SALICYLATE; CITRAL; .ALPHA.-HEXYLCINNAMALDEHYDE; WATER; GLYCERIN; CARTHAMUS TINCTORIUS SEED OLEOSOMES; PENTYLENE GLYCOL; BUTYLENE GLYCOL; ALKYL (C12-15) BENZOATE; NIACINAMIDE; STARCH, CORN; SODIUM ACRYLATE/SODIUM ACRYLOYLDIMETHYLTAURATE COPOLYMER (4000000 MW); PHENOXYETHANOL; ISOHEXADECANE; DIMETHICONE; ETHYLHEXYL METHOXYCRYLENE; POLYSORBATE 80; .ALPHA.-TOCOPHEROL ACETATE; ALOE VERA LEAF; CARBOMER INTERPOLYMER TYPE A (ALLYL SUCROSE CROSSLINKED); SORBITAN MONOOLEATE; ETHYLHEXYLGLYCERIN; GLUCONOLACTONE; TRISODIUM ETHYLENEDIAMINE DISUCCINATE; SODIUM HYDROXIDE; XANTHAN GUM; CITRIC ACID MONOHYDRATE; POTASSIUM HYDROXIDE; SODIUM BENZOATE; AGATHOSMA BETULINA LEAF; WATERMELON SEED; LIMONENE, (+)-; LINALOOL, (+/-)-

KENDO (as PLD) - FENTY SKIN HYDRA VIZOR - SPF 30 (71499-220)

ACTIVE INGREDIENTS

AVOBENZONE 3%

HOMOSALATE 9%

OCTISALATE 4.5%

PURPOSE

SUNSCREEN

USES

- HELPS PREVENT SUNBURN
- IF USED AS DIRECTED WITH OTHER SUN PROTECTION MEASURES (SEE DIRECTIONS), DECREASES THE RISK OF SKIN CANCER AND EARLY SKIN AGING CAUSED BY THE SUN.

WARNINGS

FOR EXTERNAL USE ONLY.

DO NOT USE ON DAMAGED OR BROKEN SKIN.

STOP USE AND ASK A DOCTOR IF RASH OCCURS.

WHEN USING THIS PRODUCT KEEP OUT OF EYES. RINSE WITH WATER TO REMOVE.

KEEP OUT OF REACH OF CHILDREN. IF SWALLOWED, GET MEDICAL HELP OR CONTACT A POISON CONTROL CENTER RIGHT AWAY.

DIRECTIONS

- APPLY LIBERALLY 15 MINUTES BEFORE SUN EXPOSURE.
- USE A WATER RESISTANT SUNSCREEN IF SWIMMING OR SWEATING.
- REAPPLY AT LEAST EVERY 2 HOURS.
- CHILDREN UNDER 6 MONTHS: ASK A DOCTOR.
- SUN PROTECTION MEASURES. SPENDING TIME IN THE SUN INCREASES YOUR RISK OF SKIN CANCER AND EARLY SKIN AGING. TO DECREASE THIS RISK, REGULARLY USE A SUNCREEN WITH A BROAD SPECTRUM SPF VALUE OF 15 OR HIGHER AND OTHER SUN PROTECTION MEASURES INCLUDING:
- LIMIT TIME IN THE SUN, ESPECIALLY FROM 10 A.M. - 2 P.M.
- WEAR LONG=SLEEVED SHIRTS, PANTS, HATS, AND SUNGLASSES.

OTHER INFORMATION

PROTECT THIS PRODUCT FROM EXCESSIVE HEAT AND DIRECT SUN.

INACTIVE INGREDIENTS

WATER, GLYCERIN, CARTHAMUS TINCTORIUS SEED OLEOSOMES, PENTYLENE GLYCOL, BUTYLENE GLYCOL, C12-15 ALKYL BENZOATE, NIACINAMIDE, ZEA MAYS (CORN) STARCH, HYALURONIC ACID, SODIUM HYALURONATE, CITRULLUS LANATUS (WATERMELON) SEED EXTRACT, ADANSONIA DIGITATA PULP EXTRACT, BAROSMA BETULINA LEAF EXTRACT, ALOE BARBADENSIS LEAF JUICE, TOCOPHERYL ACETATE, GLUCONOLACTONE, SORBITAN OLEATE, ACRYLATES/C10-30 ALKYL ACRYLATE CROSSPOLYMER, SODIUM ACRYLATE/SODIUM ACRYLOYLDIMETHYLTAURATE COPOLYMER, DIMETHICONE, ISOHEXADECANE, ETHYLHEXYL METHOXYCRYLENE, POLYSORBATE 80, XANTHAN GUM, SODIUM HYDROXIDE, CITRIC ACID, POTASSIUM HYDROXIDE, TOCOPHEROL, TRISODIUM ETHYLENEDIAMINE DISUCCINATE, ETHYLHEXYLGLYCERIN, SODIUM BENZOATE, POTASSIUM SORBATE, PHENOXYETHANOL, FRAGRANCE, BENZYL SALICYLATE, CITRAL, HEXYL CINNAMAL, LIMONENE, LINALOOL, RED 33.

QUESTIONS?

FENTYSKIN.COM